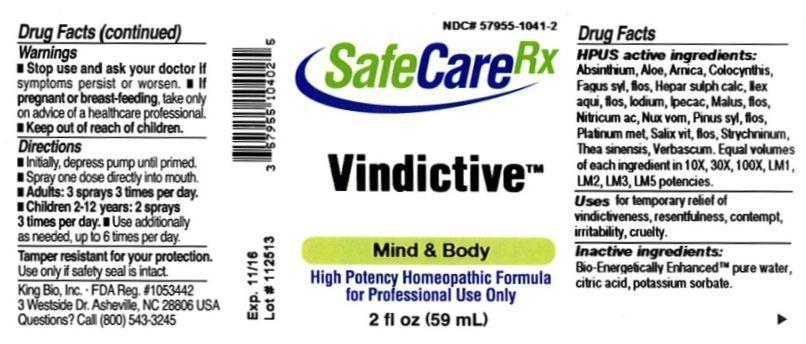 DRUG LABEL: Vindictive
NDC: 57955-1041 | Form: LIQUID
Manufacturer: King Bio Inc.
Category: homeopathic | Type: HUMAN OTC DRUG LABEL
Date: 20131218

ACTIVE INGREDIENTS: WORMWOOD 10 [hp_X]/59 mL; ALOE 10 [hp_X]/59 mL; ARNICA MONTANA 10 [hp_X]/59 mL; CITRULLUS COLOCYNTHIS FRUIT PULP 10 [hp_X]/59 mL; FAGUS SYLVATICA FLOWERING TOP 10 [hp_X]/59 mL; CALCIUM SULFIDE 10 [hp_X]/59 mL; ILEX AQUIFOLIUM FLOWERING TOP 10 [hp_X]/59 mL; IPECAC 10 [hp_X]/59 mL; MALUS DOMESTICA FLOWER 10 [hp_X]/59 mL; NITRIC ACID 10 [hp_X]/59 mL; STRYCHNOS NUX-VOMICA SEED 10 [hp_X]/59 mL; PINUS SYLVESTRIS FLOWERING TOP 10 [hp_X]/59 mL; PLATINUM 10 [hp_X]/59 mL; SALIX ALBA FLOWERING TOP 10 [hp_X]/59 mL; STRYCHNINE 10 [hp_X]/59 mL; GREEN TEA LEAF 10 [hp_X]/59 mL; VERBASCUM THAPSUS 10 [hp_X]/59 mL
INACTIVE INGREDIENTS: WATER; CITRIC ACID MONOHYDRATE; POTASSIUM SORBATE

Vindictive

Drug Facts

____________________________________________________________________________________________________________________

HPUS active ingredients: Absinthium, Aloe socotrina, Arnica montana, Colocynthis, Fagus sylvatica, flos, Hepar sulphuris calcareum, Ilex aquifolium, flos, Ipecacuanha, Malus pumila, flos, Nitricum acidum, Nux vomica, Pinus sylvestris, flos, Platinum metallicum, Salix vitellina, flos, Strychninum, Thea sinensis, Verbascum thapsus. Equal volumes of each ingredient in 10X, 30X, 100X, LM1, LM2, LM3, LM5 potencies.

INDICATIONS AND USAGE

Uses for temporary relief of vindictiveness, resentfulness, contempt, irritability, cruelty.

INACTIVE INGREDIENT

Inactive ingredients: Bio-Energetically Enhanced pure water, citric acid, potassium sorbate.

Warnings

- Stop use and ask your doctor if symptoms persist or worsen.
- If pregnant or breast-feeding, take only on advice of a healthcare professional.

- Keep out of reach of children.

Directions:

- Initially, depress pump until primed.
- Spray one dose directly into mouth.
- Adults: 3 sprays 3 times per day.
- Children 2-12 years: 2 sprays 3 times per day.
- Use additionally as needed, up to 6 times per day.

OTHER SAFETY INFORMATION

Tamper resistant for your protection. Use only if safety seal is intact.

PURPOSE

Uses for temporary relief of:

- vindictiveness
- resentfulness
- contempt
- irritability
- cruelty